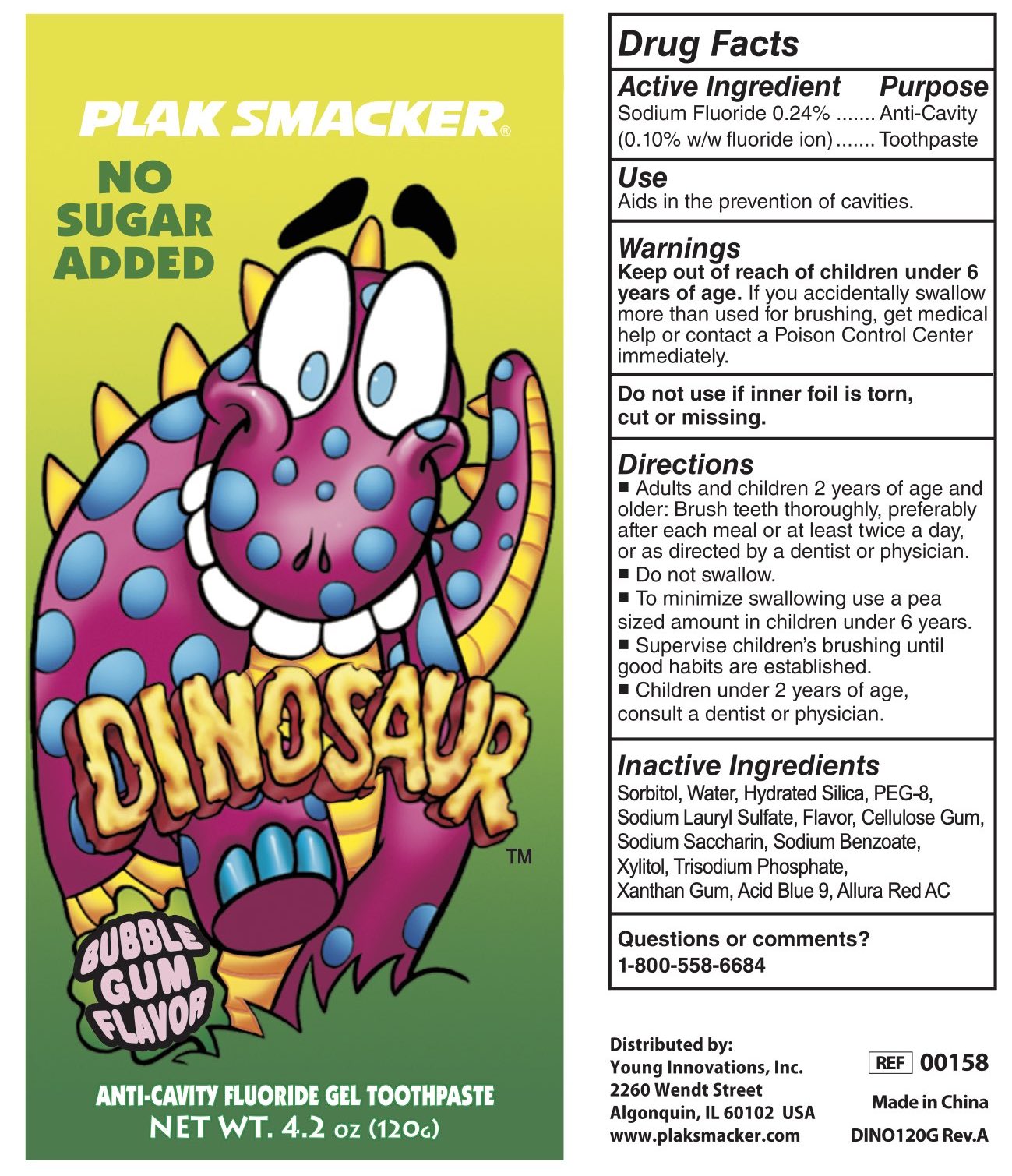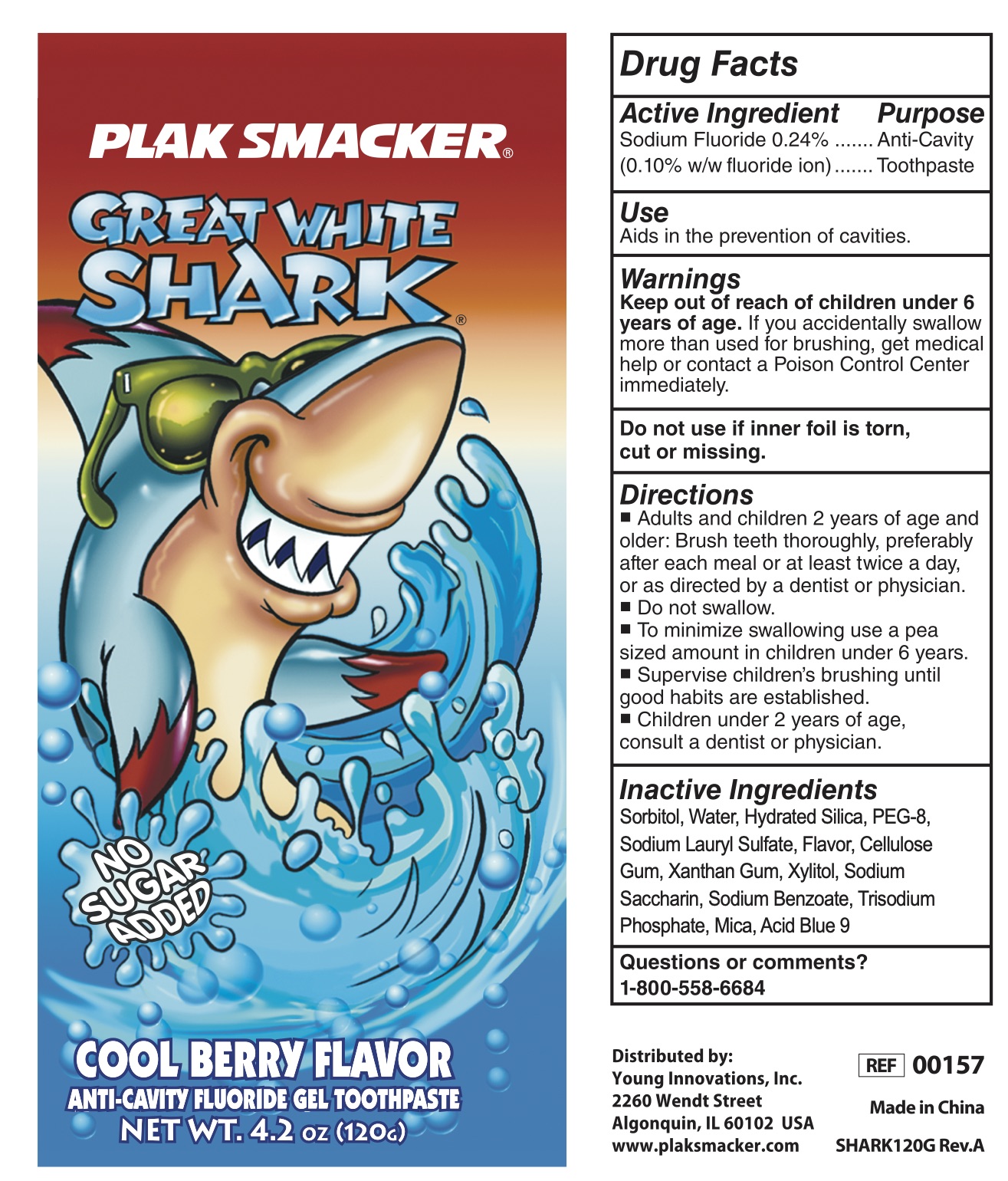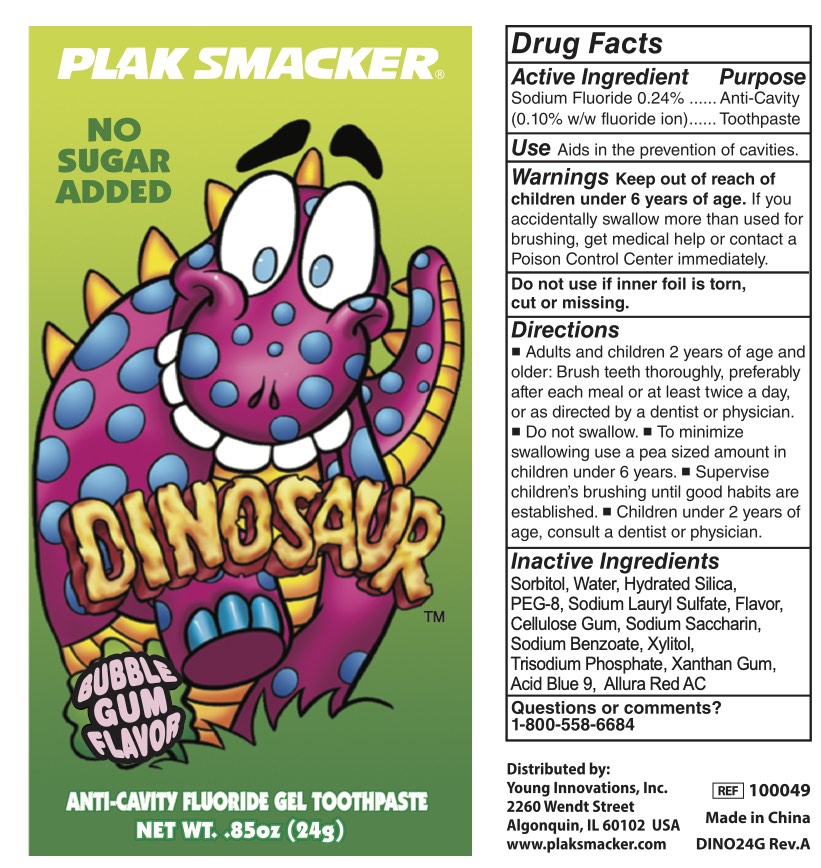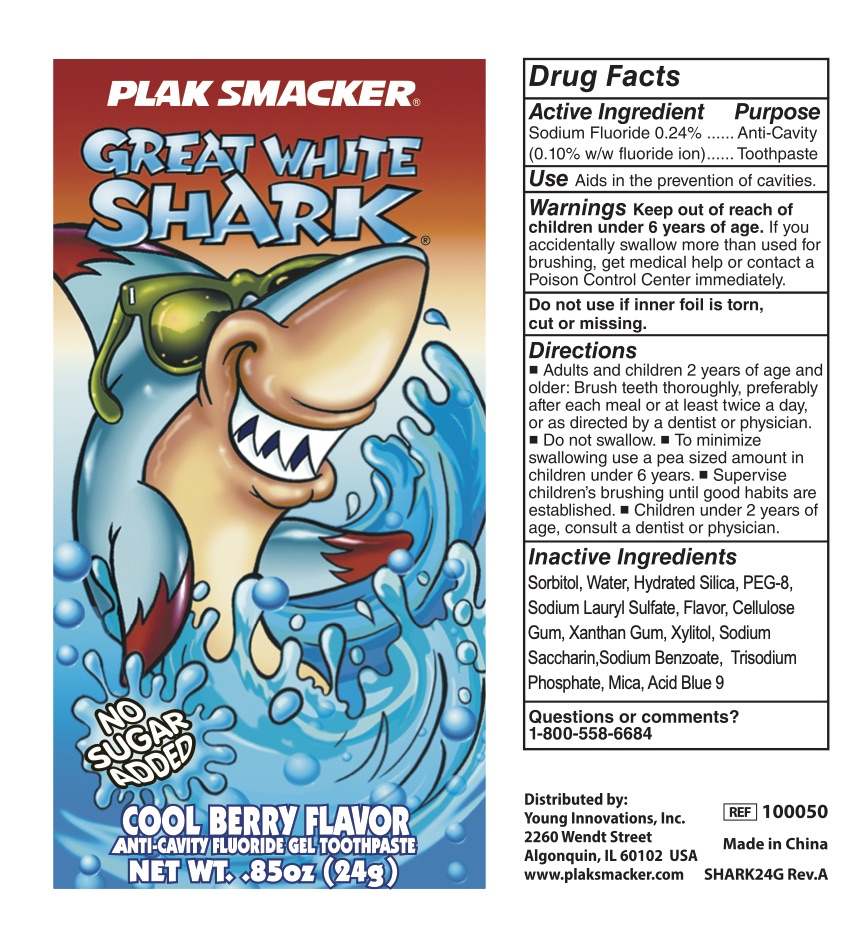 DRUG LABEL: dinosaur
NDC: 71775-070 | Form: PASTE
Manufacturer: LMZ
Category: otc | Type: HUMAN OTC DRUG LABEL
Date: 20210501

ACTIVE INGREDIENTS: SODIUM FLUORIDE 100 mg/100 g
INACTIVE INGREDIENTS: POLYETHYLENE GLYCOL 400; WATER; HYDRATED SILICA; TITANIUM DIOXIDE; CARBOXYMETHYLCELLULOSE; SODIUM CHLORIDE; SACCHARIN SODIUM; SODIUM PHOSPHATE, TRIBASIC, ANHYDROUS; SORBITOL; ZANTHOXYLUM NITIDUM ROOT; SODIUM BICARBONATE; SODIUM LAUROYL SARCOSINATE; BENZYL ALCOHOL; SODIUM COPPER CHLOROPHYLLIN; ETHYL MENTHANE CARBOXAMIDE; CLINOPODIUM CHINENSE WHOLE; CHONDRUS CRISPUS

Plak Smacker

Active Ingredients

Sodium Fluoride 0.24% Anti-Cavity
(0.10% w/w fluoride ion) Toothpaste

Purpose

Anti-Cavity
Toothpaste

Use

Aids in the prevention of cavities.

Warnings

If you accidentally swallow
more than used for brushing, get medical
help or contact a Poison Control Center
immediately.

Keep out of reach of children under 6 years of age.

Do not use if inner foil is torn, cut or missing.

Directions

Adults and children 2 years of age and older: Brush teeth thoroughly, preferably after each meal or at least twice a day, or as directed by a dentist or physician.

- Do not swallow.
- To minimize swallowing use a pea sized amount in children under 6 years.
- Supervise children’s brushing until good habits are established.
- Children under 2 years of age, consult a dentist or physician.

Inactive Ingredients

Sorbitol, Water, Hydrated Silica, PEG-8, Sodium Lauryl Sulfate, Flavor, Cellulose Gum, Sodium Saccharin, Sodium Benzoate, Xylitol, Trisodium Phosphate, Xanthan Gum, Acid Blue 9, Allura Red AC

Questions or comments?

1-800-558-6684

PACKAGE LABEL

24g NDC: 71775-070-54

120g NDC: 71775-070-52

24g NDC: 71775-070-55

120g NDC: 71775-070-53